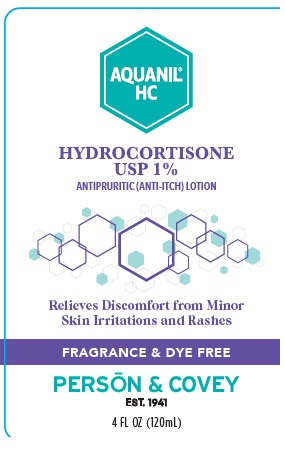 DRUG LABEL: Aquanil HC
NDC: 0096-0732 | Form: LOTION
Manufacturer: Person and Covey
Category: otc | Type: HUMAN OTC DRUG LABEL
Date: 20251129

ACTIVE INGREDIENTS: HYDROCORTISONE 0.01 g/1 g
INACTIVE INGREDIENTS: BENZYL ALCOHOL; WATER; SODIUM LAURYL SULFATE; XANTHAN GUM; GLYCERIN; CETYL ALCOHOL; STEARYL ALCOHOL

Aquanil HC

Active Ingredient

Hydrocortisone

Stop use and ask a doctor if:

-Condition worsens

-If symptoms persit for more than 7 days or clear up and occur again within a few days. Discocntinue use of this product and do not begin use of any other hydrocortisone product unless you have consulted a doctor.

-Do no use for diaper rash. Consult a doctor.

Keep out of the reach of children. If swallowed, get medical help or contact Poison Control Center right away.

Purpose

Antipruritic (Anti-itch)

Directions

-Shake will before using.

-For adults and children 2 years of age and older: Apply to affected area not more than 2 to 4 times daily.

-For children under 2 years of age: there is no recommended dosage except under the advice and supervision of a ddoctor.

-Store away from excessive heat or cold.

Inactive Ingredients

Purified Water, Glycerin, Cetyl Alcohol, Benzyl Alcohol, Sodium Laureth Sulfate, Stearyl Alcohol, Simethicone, Xanthan Gum

Questions?

Questions? Please call (800) 423-2341

Uses

For the temporary relief of minor skin irritations, inflamaations, itching and rashes caused by:

-insect bites

-eczema

-psoriasis

-soaps

-detergents

-cosmetics,

-jewelry,

-poison oak,

-poison sumac

-Other uses of this product should be undertaken only under the advice and supervision of a doctor.

Warnings

For external use only.

Do not get into eyes. If contact occurs, rinse thoroughly with water.